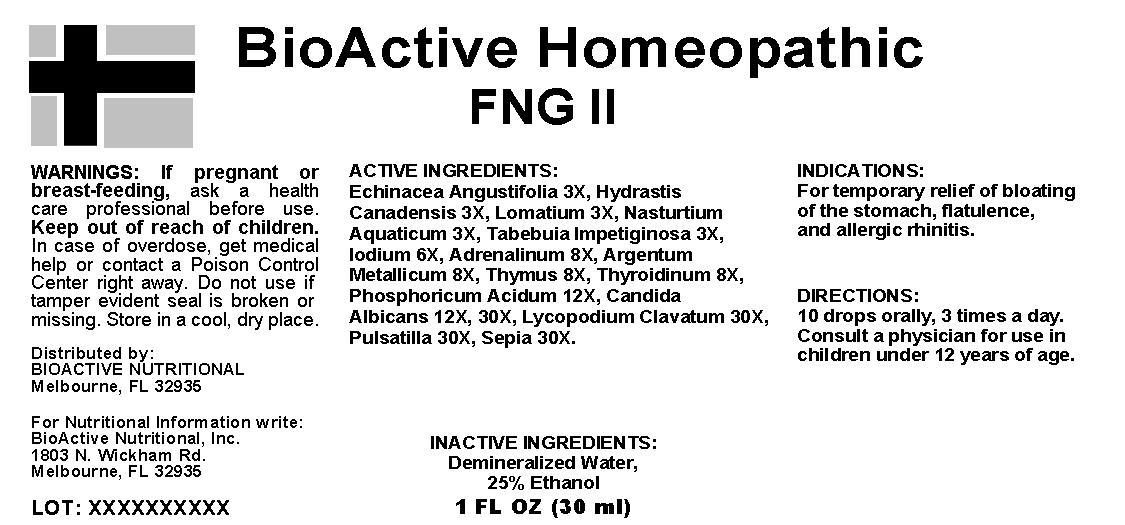 DRUG LABEL: FNG 
NDC: 57520-0099 | Form: LIQUID
Manufacturer: Apotheca Company
Category: homeopathic | Type: HUMAN OTC DRUG LABEL
Date: 20150820

ACTIVE INGREDIENTS: ECHINACEA ANGUSTIFOLIA 3 [hp_X]/1 mL; GOLDENSEAL 3 [hp_X]/1 mL; LOMATIUM DISSECTUM ROOT 3 [hp_X]/1 mL; TABEBUIA IMPETIGINOSA BARK 3 [hp_X]/1 mL; IODINE 6 [hp_X]/1 mL; EPINEPHRINE 8 [hp_X]/1 mL; SILVER 8 [hp_X]/1 mL; SUS SCROFA THYMUS 8 [hp_X]/1 mL; THYROID, UNSPECIFIED 8 [hp_X]/1 mL; PHOSPHORIC ACID 12 [hp_X]/1 mL; CANDIDA ALBICANS 30 [hp_X]/1 mL; LYCOPODIUM CLAVATUM SPORE 30 [hp_X]/1 mL; PULSATILLA VULGARIS 30 [hp_X]/1 mL; SEPIA OFFICINALIS JUICE 30 [hp_X]/1 mL; RORIPPA NASTURTIUM-AQUATICUM 3 [hp_X]/1 mL
INACTIVE INGREDIENTS: WATER; ALCOHOL

Drug Facts:

ACTIVE INGREDIENT

Active Ingredients: Echinacea Angustifolia 3X, Hydrastis Canadensis 3X, Lomatium 3X, Nasturtium Aquaticum 3X, Tabebuia Impetiginosa 3X, Iodium 6X, Adrenalinum 8X, Argentum Metallicum 8X, Thymus 8X, Thyroidinum 8X, Phosphoricum Acidum 12X, Candida Albicans 12X, 30X, Lycopodium Clavatum 30X, Pulsatilla 30X, Sepia 30X.

PURPOSE

Indications: For temporary relief of bloating of the stomach, flatulence, and allergic rhinitis.

WARNINGS

WARNINGS: If pregnant or breast-feeding, ask a health care professional before use.

Keep our of reach of children. In case of overdose, get medical help or contact a Poison Control Center right away.

Do not use if tamper evident seal is broken or missing.

Store in a cool, dry place.

KEEP OUT OF REACH OF CHILDREN:

Keep our of reach of children. In case of overdose, get medical help or contact a Poison Control Center right away.

DOSAGE AND ADMINISTRATION

Directions: 10 drops orally, 3 times a day. Consult a physician for use in children under 12 years of age.

INDICATIONS & USAGE SECTION:

For temporary relief of bloating of the stomach, flatulence, and allergic rhinitis.

Inactive Ingredients: Demineralized Water, 25% Ethanol

QUESTIONS

Distributed By:

BioActive Nutritional

Melbourne, FL 32935

For Nutritional Information Write:

BioActive Nutritional, Inc.

1803 N Wickham Rd.

Melbourne, FL 32935

PACKAGE LABEL

BioActive Homeopathic

FNG II

1 FL OZ (30 ML)